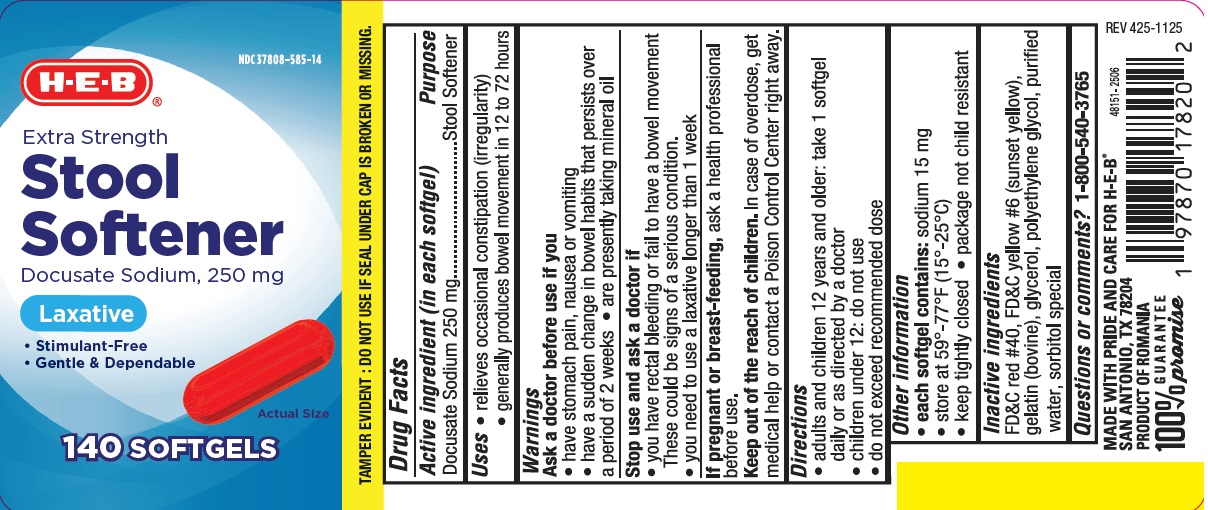 DRUG LABEL: Stool Softener
NDC: 37808-585 | Form: CAPSULE, LIQUID FILLED
Manufacturer: HEB
Category: otc | Type: HUMAN OTC DRUG LABEL
Date: 20251209

ACTIVE INGREDIENTS: DOCUSATE SODIUM 250 mg/1 1
INACTIVE INGREDIENTS: GELATIN; GLYCERIN; FD&C YELLOW NO. 6; WATER; FD&C RED NO. 40; POLYETHYLENE GLYCOL, UNSPECIFIED; SORBITOL

heb425S

Active ingredient (in each softgel)

Docusate Sodium 250 mg

Purpose

Stool Softener

Uses

- relieves occasional constipation (irregularity)
- generally produces bowel movement in 12 to 72 hours

Warnings

Ask a doctor before use if you

- have stomach pain, nausea, or vomiting
- have a sudden change in bowel habits that persists over a period of 2 weeks
- are presently taking mineral oil

Stop use and ask a doctor if

- you need to use a laxative longer than 1 week
- you have rectal bleeding or fail to have a bowel movement.

These could be signs of a serious condition.

If pregnant or breast-feeding, ask a health professional before

use.

Keep out of reach of children. In case of overdose , get medical help or contact a Poison Control Center right away.

Directions

- adults and children 12 years and older: take 1 softgel daily or as directed by a doctor
- children under 12: do not use
- do not exceed recommended dose

Other information

- each softgel contains: sodium 15 mg
- store at 59°-77°F (15°-25°C)
- keep tightly closed
- package not child resistant

Inactive ingredients

FD&C red #40, FD&C yellow #6 (sunset yellow), gelatin (bovine), glycerol, polyethylene glycol, purified water, sorbitol special

Questions or comments?

1-800-540-3765